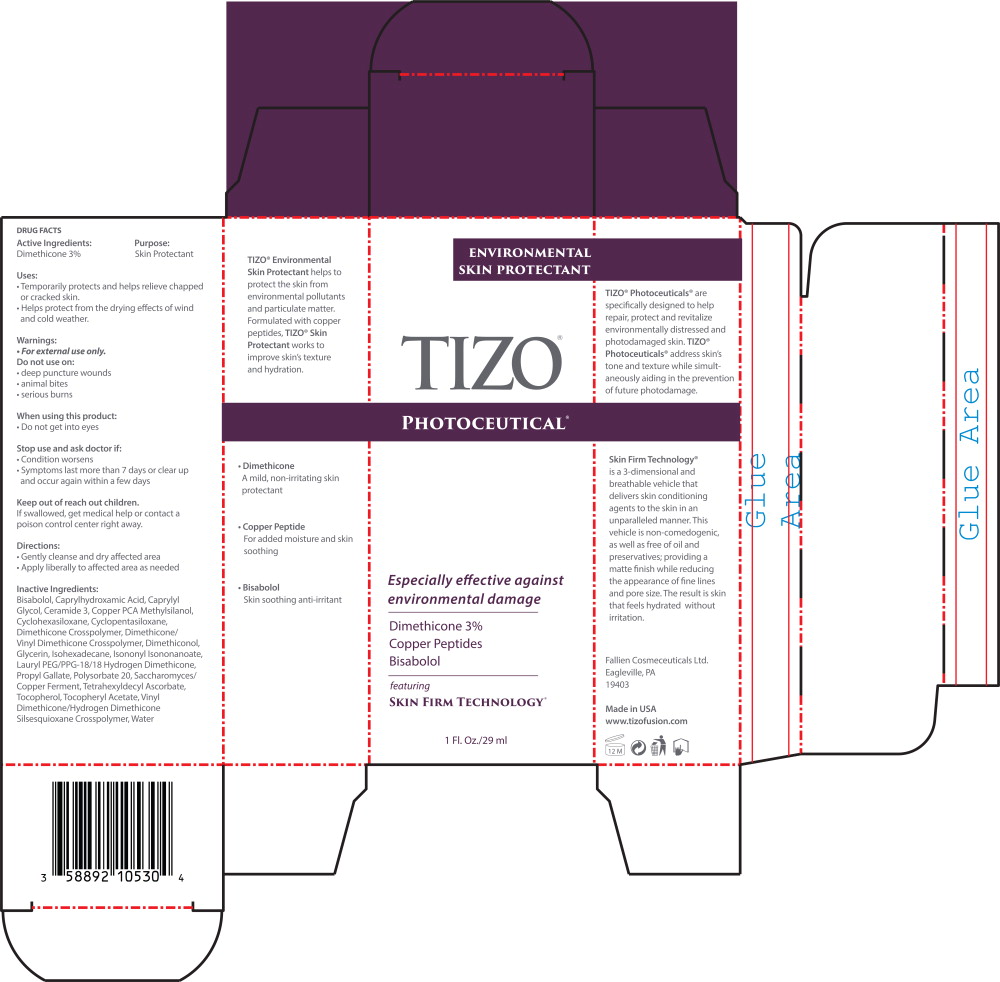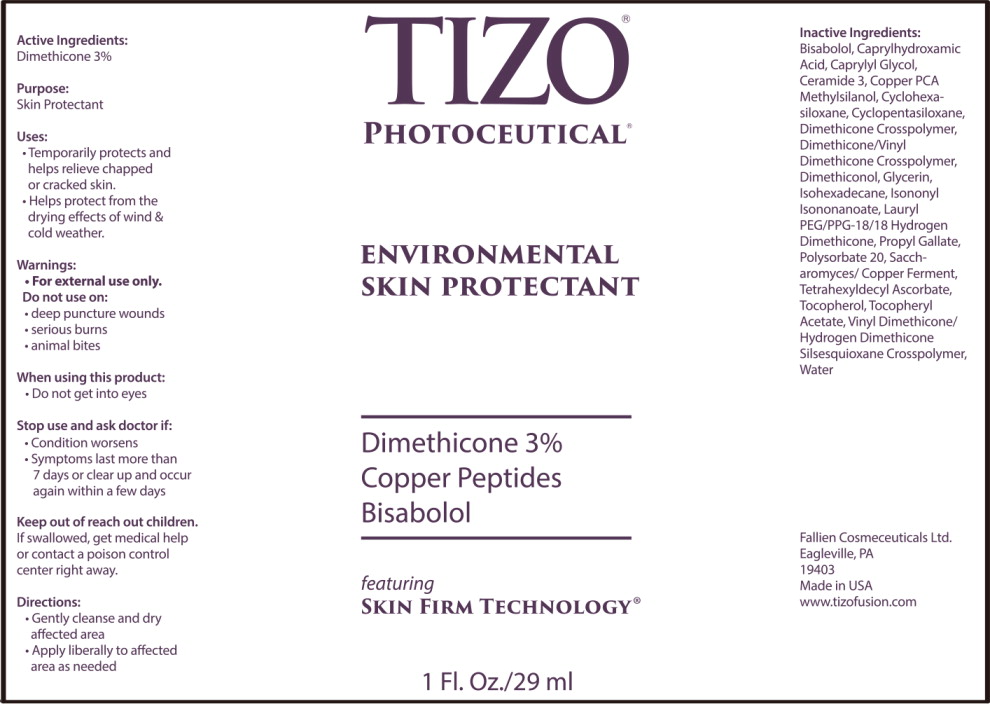 DRUG LABEL: TiZO Photoceutical Environmental Skin Protectant
NDC: 58892-105 | Form: GEL
Manufacturer: Fallien Cosmeceuticals, LTD
Category: otc | Type: HUMAN OTC DRUG LABEL
Date: 20241114

ACTIVE INGREDIENTS: DIMETHICONE 30 mg/1 mL
INACTIVE INGREDIENTS: .ALPHA.-BISABOLOL, (+/-)-; CAPRYLHYDROXAMIC ACID; CAPRYLYL GLYCOL; CERAMIDE NP; COPPER PIDOLATE; METHYLSILANOL PCA; CYCLOMETHICONE 6; CYCLOMETHICONE 5; DIMETHICONE CROSSPOLYMER (450000 MPA.S AT 12% IN CYCLOPENTASILOXANE); DIMETHICONE/VINYL DIMETHICONE CROSSPOLYMER (SOFT PARTICLE); DIMETHICONOL (2000 CST); GLYCERIN; ISOHEXADECANE; ISONONYL ISONONANOATE; LAURYL PEG/PPG-18/18 METHICONE; PROPYL GALLATE; POLYSORBATE 20; SACCHAROMYCES CEREVISIAE; TETRAHEXYLDECYL ASCORBATE; .ALPHA.-TOCOPHEROL ACETATE; VINYL DIMETHICONE/METHICONE SILSESQUIOXANE CROSSPOLYMER; WATER

DRUG FACTS

Active Ingredients:

Dimethicone 3%

Purpose:

Skin Protectant

Uses:

- Temporarily protects and helps relieve chapped or cracked skin.
- Helps protect from the drying effects of wind and cold weather.

Warnings:

- For external use only.

Do not use on:

- deep puncture wounds
- animal bites
- serious burns

When using this product:

- Do not get into eyes

Stop use and ask doctor if:

- Condition worsens
- Symptoms last more than 7 days or clear up and occur again within a few days

Keep out of reach out children.

If swallowed, get medical help or contact a poison control center right away.

Directions:

- Gently cleanse and dry affected area
- Apply liberally to affected area as needed

Inactive Ingredients:

Bisabolol, Caprylhydroxamic Acid, Caprylyl Glycol, Ceramide 3, Copper PCA Methylsilanol, Cydohexasiloxane, Cyclopentasiloxane, Dimethicone Crosspolymer, Dimethicone/Vinyl Dimethicone Crosspolymer, Dimethiconol, Glycerin, Isohexadecane, Isononyl Isononanoate, Lauryl PEG/PPG-18/18 Hydrogen Dimethicone, Propyl Gallate, Polysorbate 20, Saccharomyces/ Copper Ferment, Tetrahexyldecyl Ascorbate, Tocopherol, Tocopheryl Acetate, Vinyl Dimethicone/Hydrogen Dimethicone Silsesquioxane Crosspolymer, Water

Keep out of the reach of children.

Principal Display Panel – Carton Label

ENVIRONMENTAL

SKIN PROTECTANT

TIZO®

PHOTOCEUTICAL®

Especially effective against
environmental damage

Dimethicone 3%

Copper Peptides

Bisabolol

featuring

SKIN FIRM TECHNOLOGY®

1 Fl. Oz./29 ml

Principal Display Panel – Bottle Label

TIZO®

PHOTOCEUTICAL®

ENVIRONMENTAL

SKIN PROTECTANT

Dimethicone 3%

Copper Peptides

Bisabolol

featuring

SKIN FIRM TECHNOLOGY®

1 Fl. Oz./29 ml